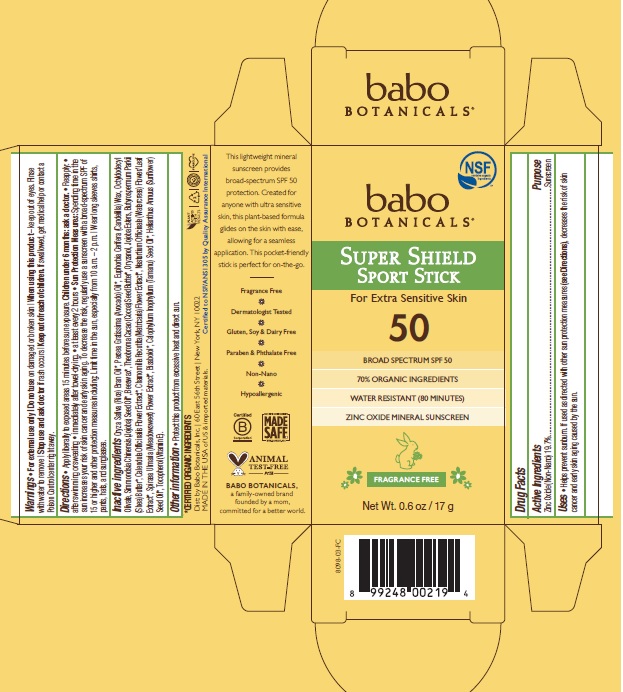 DRUG LABEL: Babo Botanicals Super Shield Sport Sunscreen SPF 50
NDC: 79265-8908 | Form: STICK
Manufacturer: Babo Botanicals, Inc.
Category: otc | Type: HUMAN OTC DRUG LABEL
Date: 20241212

ACTIVE INGREDIENTS: ZINC OXIDE 197 mg/1 g
INACTIVE INGREDIENTS: CALENDULA OFFICINALIS FLOWER; NASTURTIUM OFFICINALE; FILIPENDULA ULMARIA FLOWER; RICE BRAN OIL; SHEA BUTTER; SUNFLOWER OIL; HYDROGENATED JOJOBA OIL, RANDOMIZED; AVOCADO OIL; JOJOBA OIL; ORYZANOL; CANDELILLA WAX; OCTYLDODECYL OLEATE; TOCOPHEROL; LEVOMENOL; TAMANU OIL; COCOA BUTTER; CHAMOMILE

8908 Babo Botanicals Super Shield Sport Stick Sunscreen SPF 50

Active Ingredient

Zinc Oxide (Non-Nano) 19.7%

Uses

- Helps prevent sunburn. If used as directed with other sun protection measures (see Directions), decreases the risk of skin cancer and early skin aging caused by the sun.

Purpose

Sunscreen

Warnings

For external use only

Do not use

on damaged or broken skin.

When using this product

keep out of eyes. Rinse with water to remove.

Stop use and ask doctor

if rash occurs

Keep out of reach of children

If swallowed, get medical help or contact a Poison Control center right away.

Directions

- Apply liberally to exposed areas 15 minutes before sun exposure. Children under 6 months: ask a doctor.
- Reapply
- after swimming or sweating
- immediately after towel-drying
- at least every 2 hours
- Sun Protection Measures: Spending time increases your risk of skin cancer and early skin aging. To decrease the risk, regularly use a sunscreen with a broad-spectrum SPF of 15 or higher and other protection measures including: Limit time in the sun, especially from 10 a.m. - 2 p.m. Wear long sleeves shirts, pants, hats, and sunglasses.

Inactive ingredients

Oryza Sativa (Rice) Bran Oil*, Persea Gratissima (Avocado) Oil*, Euphorbia Cerifera (Candelilla) Wax, Octyldodecyl Olivate, Simmondsia Chinensis (Jojoba) Seed Oil*, Beeswax*, Theobroma Cacao (Cocoa) Seed Butter*, Oryzanol, Jojoba Esters, Butyrospermum Parkii (Shea) Butter*, Calendula Officinalis Flower Extract*, Chamomilla Recutita (Matricaria) Flower Extract*, Nasturtium Officinale (Watercress) Flower/Leaf Extract*, Spiraea Ulmaria (Meadowsweet) Flower Extract*, Bisabolol*, Calophyllum Inophyllum (Tamanu) Seed Oil*, Helianthus Annuus (Sunflower) Seed Oil*, Tocopherol (Vitamin E).

*Certified Organic ingredients

Other information

Protect this product from excessive heat and direct sun.

Company Information

Dist. by Babo Botanicals, Inc. 60 East 56th Street

New York, NY 10022